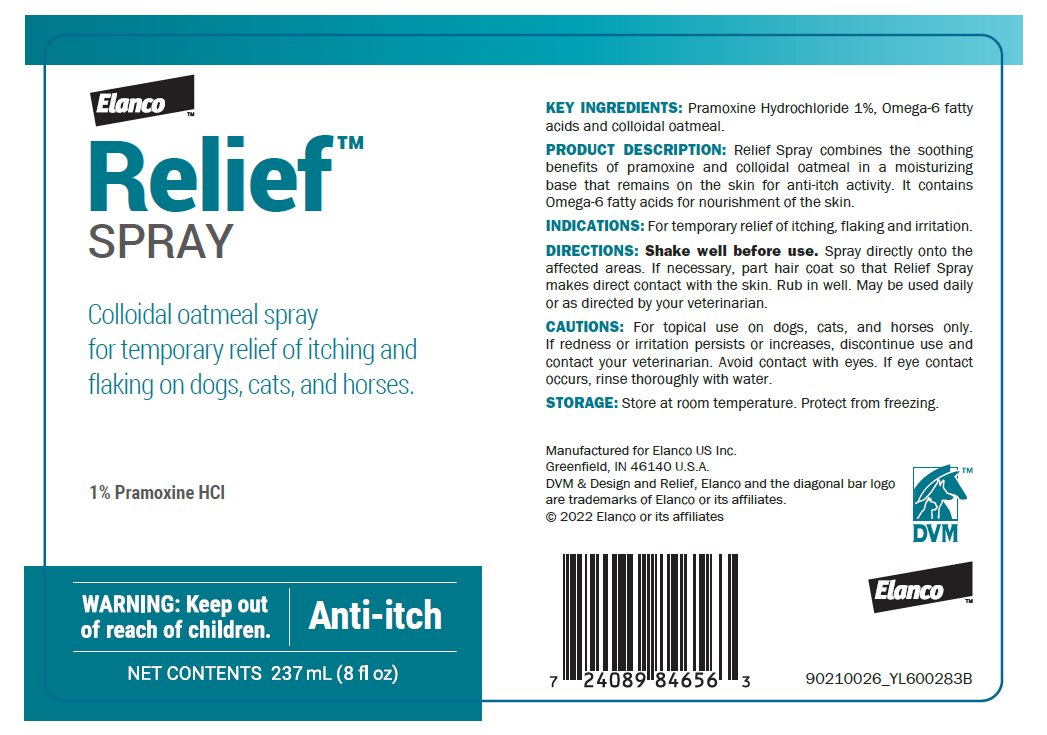 DRUG LABEL: Relief
NDC: 58198-0014 | Form: SPRAY
Manufacturer: Elanco US Inc.
Category: animal | Type: OTC ANIMAL DRUG LABEL
Date: 20230412

ACTIVE INGREDIENTS: PRAMOXINE HYDROCHLORIDE 10.8 mg/1 mL

KEY INGREDIENTS: Pramoxine Hydrochloride 1%, Omega-6 fatty acids and colloidal oatmeal.

DESCRIPTION

PRODUCT DESCRIPTION: Relief Spray combines the soothing benefits of pramoxine and colloidal oatmeal in a moisturizing base that remains on the skin for anti-itch activity. It contains Omega-6 fatty acids for nourishment of the skin.

INDICATIONS AND USAGE

INDICATIONS: For temporary relief of itching, flaking and irritation.

DOSAGE AND ADMINISTRATION

DIRECTIONS: Shake well before use. Spray directly onto the affected areas. If necessary, part hair coat so that Relief Spray makes direct contact with the skin. Rub in well. May be used daily or as directed by your veterinarian.

CAUTIONS: For topical use on dogs, cats, and horses only. If redness or irritation persists or increases, discontinue use and contact your veterinarian. Avoid contact with eyes. If eye contact occurs, rinse thoroughly with water.

STORAGE: Store at room temperature. Protect from freezing.

Manufactured for Elanco US Inc.
Greenfield, IN 46140 U.S.A.
DVM & Design and Relief, Elanco and the diagonal bar logo
are trademarks of Elanco or its affiliates.
© 2022 Elanco or its affiliates

DVM™

Elanco™

90210026_YL600283B

Principal Display Panel – 237 mL Bottle Spray Label

Elanco™

Relief™
SPRAY

Colloidal oatmeal spray
for temporary relief of itching and
flaking on dogs, cats, and horses.

1% Pramoxine HCl

WARNING: Keep out of reach of children.

Anti-itch

NET CONTENTS 237mL (8 fl oz)